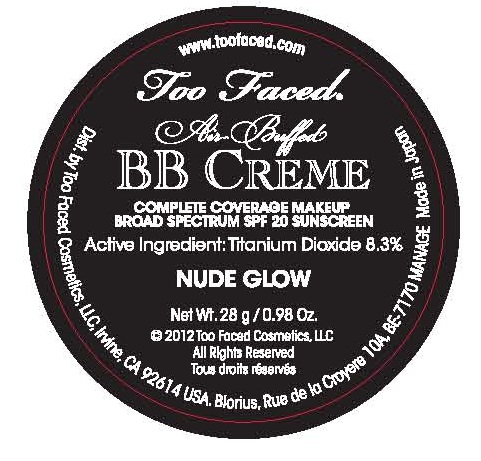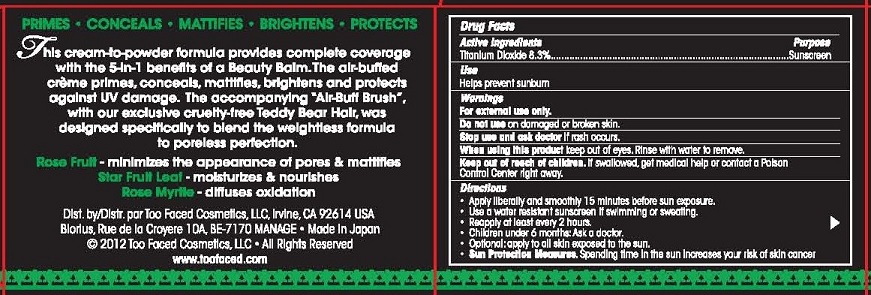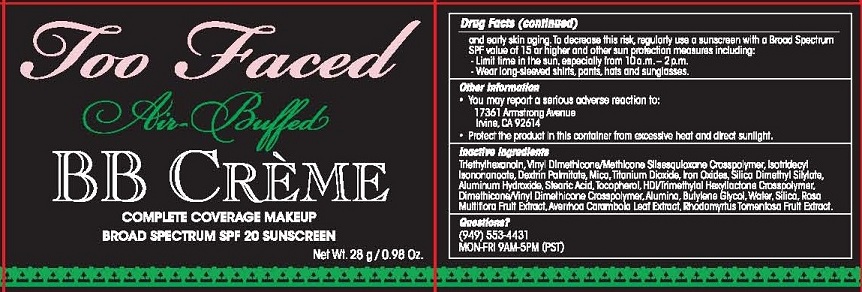 DRUG LABEL: Too Faced BB Creme Complete Coverage Make-Up
NDC: 79596-100 | Form: CREAM
Manufacturer: TOO FACED COSMETICS
Category: otc | Type: HUMAN OTC DRUG LABEL
Date: 20121218

ACTIVE INGREDIENTS: TITANIUM DIOXIDE 8.3 g/100 g
INACTIVE INGREDIENTS: TRIETHYLHEXANOIN; DIMETHICONE/VINYL DIMETHICONE CROSSPOLYMER; ISOTRIDECYL ISONONANOATE; DECYL PALMITATE; MICA; FERRIC OXIDE RED; SILICA DIMETHYL SILYLATE; ALUMINUM HYDROXIDE; STEARIC ACID; TOCOPHEROL; PIVALIC ACID; ALUMINUM OXIDE; BUTYLENE GLYCOL; WATER; SILICON DIOXIDE; ROSA MULTIFLORA FRUIT; AVERRHOA CARAMBOLA LEAF; RHODOMYRTUS TOMENTOSA FRUIT

ACTIVE INGREDIENTS

TITANIUM DIOXIDE 8.3%

PURPOSE

SUNSCREEN

USE

HELPS PREVENT SUNBURN

WARNINGS

FOR EXTERNAL USE ONLY

DO NOT USE ON DAMAGED OR BROKEN SKIN.

STOP USE AND ASK DOCTOR IF RASH OCCURS.

WHEN USING THIS PRODUCT KEEP OUT OF EYES. RINSE WITH WATER TO REMOVE.

KEEP OUT OF REACH OF CHILDREN. IF SWALLOWED, GET MEDICAL HELP OR CONTACT A POISON CONTROL CENTER RIGHT AWAY.

DIRECTIONS

- APPLY LIBERALLY AND SMOOTHLY 15 MINUTES BEFORE SUN EXPOSURE.
- USE A WATER RESISTANT SUNSCREEN IF SWIMMING OR SWEATING.
- REAPPLY AT LEAST EVERY 2 HOURS.
- CHILDREN UNDER 6 MONTHS: ASK A DOCTOR.
- OPTIONAL: APPLY TO ALL SKIN EXPOSED TO THE SUN.
- SUN PROTECTION MEASURES. SPENDING TIME IN THE SUN INCREASES YOUR RISK OF SKIN CANCER AND EARLY SKIN AGING. TO DECREASE THIS RISK, REGULARLY USE A SUNSCREEN WITH A BROAD SPECTRUM SPF OF 15 OR HIGHER AND OTHER SUN PROTECTION MEASURES INCLUDING:
- LIMIT TIME IN THE SUN, ESPECIALLY FROM 10 A.M. - 2 P.M.
- WEAR LONG-SLEEVED SHIRTS, PANTS, HATS AND SUNGLASSES.

OTHER INFORMATION

- YOU MAY REPORT A SERIOUS ADVERSE REACTION TO:
  17361 ARMSTRONG AVENUE
  IRVINE, CA 92614
- PROTECT THE PRODUCT IN THIS CONTAINER FROM EXCESSIVE HEAT AND DIRECT SUNLIGHT.

INACTIVE INGREDIENTS

TRIETHYLHEXANOIN, VINYL DIMETHICONE/METHICONE SILSESQUIOXANE CROSSPOLYMER, ISOTRIDECYL ISONONANOATE, DEXTRIN PALMITATE, MICA, TITANIUM DIOXIDE, IRON OXIDES, SILICA DIMETHYL SILYLATE, ALUMINUM HYDROXIDE, STEARIC ACID, TOCOPHEROL, HDI/TRIMETHYLOL HEXYLLACTONE CROSSPOLYMER, DIMETHICONE/VINYL DIMETHICONE CROSSPOLYMER, ALUMINA, BUTYLENE GLYCOL, WATER, SILICA, ROSA MULTIFLORA FRUIT EXTRACT, AVERRHOA CARAMBOLA LEAF EXTRACT, RHODOMYRTUS TOMENTOSA FRUIT EXTRACT.

QUESTIONS?

(949) 553-4431

MON-FRI 9AM-5PM (PST)